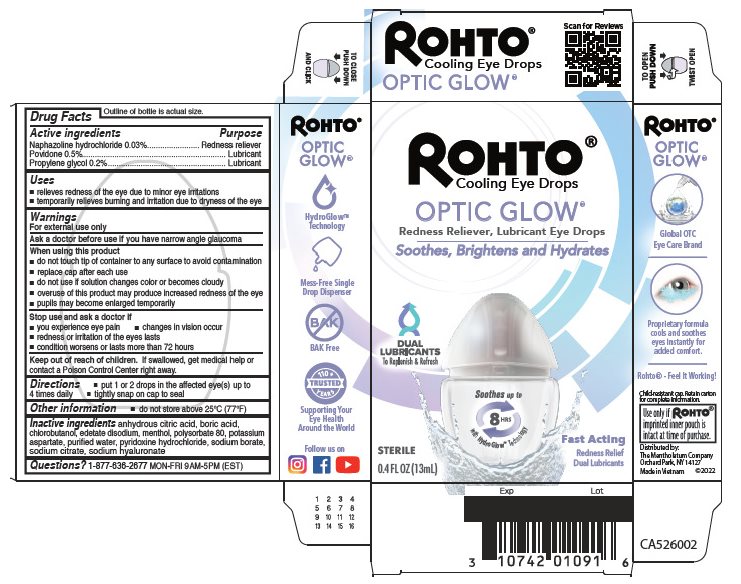 DRUG LABEL: Rohto Optic Glow
NDC: 10742-8160 | Form: LIQUID
Manufacturer: The Mentholatum Company
Category: otc | Type: HUMAN OTC DRUG LABEL
Date: 20241217

ACTIVE INGREDIENTS: NAPHAZOLINE HYDROCHLORIDE 0.3 mg/1 mL; POVIDONE, UNSPECIFIED 5 mg/1 mL; PROPYLENE GLYCOL 2 mg/1 mL
INACTIVE INGREDIENTS: ANHYDROUS CITRIC ACID; BORIC ACID; CHLOROBUTANOL; EDETATE DISODIUM; MENTHOL, UNSPECIFIED FORM; POLYSORBATE 80; POTASSIUM ASPARTATE; WATER; PYRIDOXINE HYDROCHLORIDE; SODIUM BORATE; SODIUM CITRATE, UNSPECIFIED FORM; HYALURONATE SODIUM

Drug Facts - Rohto Optic Glow

Active ingredients

Naphazoline hydrochloride 0.03%

Povidone 0.5%

Propylene glycol 0.2%

Purpose

Naphazoline hydrochloride - Redness reliever

Povidone – Lubricant

Propylene glycol - Lubricant

Uses

- relieves redness of the eye due to minor eye irritations
- temporarily relieves burning and irritation due to dryness of the eye

Warnings

For external use only

Ask a doctor before use if you have

narrow angle glaucoma

When using this product

- do not touch tip of container to any surface to avoid contamination
- replace cap after each use
- do not use if solution changes color or becomes cloudy
- overuse of this product may produce increased redness of the eye
- pupils may become enlarged temporarily

Stop use and ask a doctor if

- you experience eye pain
- changes in vision occur
- redness or irritation of the eyes lasts
- condition worsens or lasts more than 72 hours

Keep out of reach of children.

If swallowed, get medical help or contact a Poison Control Center right away.

Directions

- put 1 or 2 drops in the affected eye(s) up to 4 times daily
- tightly snap on cap to seal

Other Safety Information

- do not store above 25°C (77°F)

Inactive ingredients

anhydrous citric acid, boric acid, chlorobutanol, edetate disodium, menthol, polysorbate 80, potassium aspartate, purified water, pyridoxine hydrochloride, sodium borate, sodium citrate, sodium hyaluronate

Questions?

1-877-636-2677 MON-FRI 9 AM to 5 PM (EST)